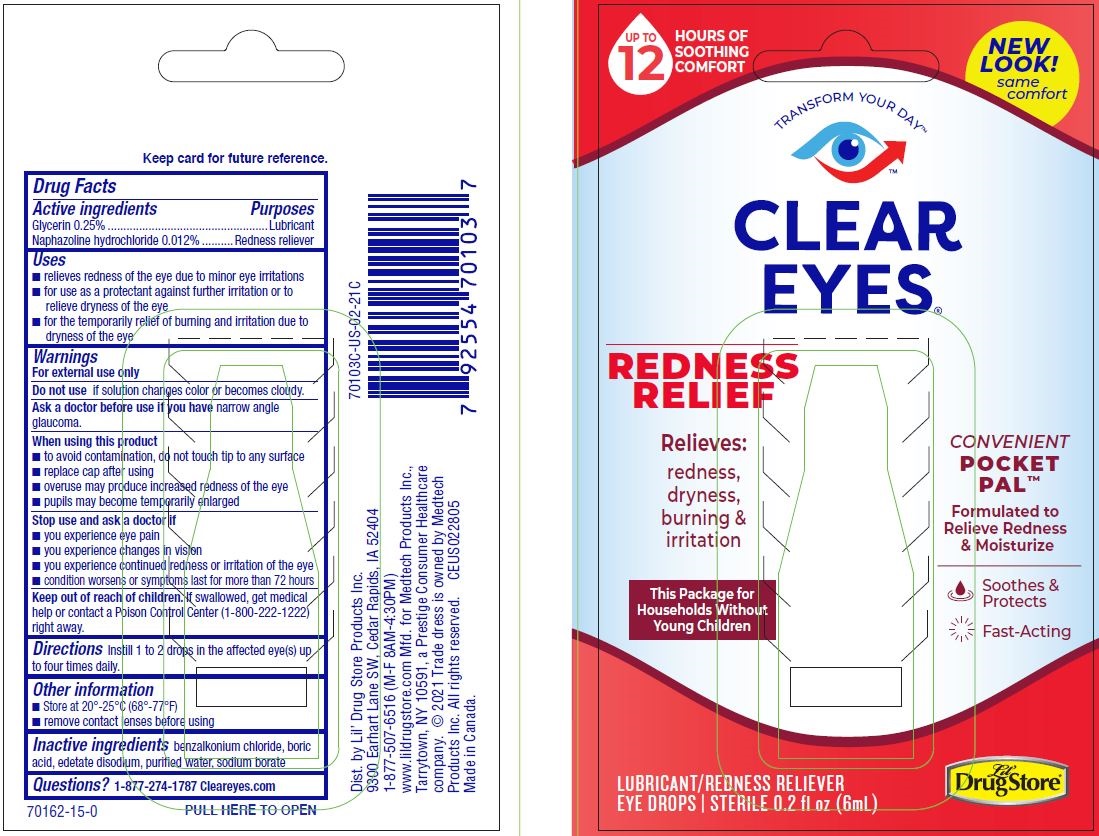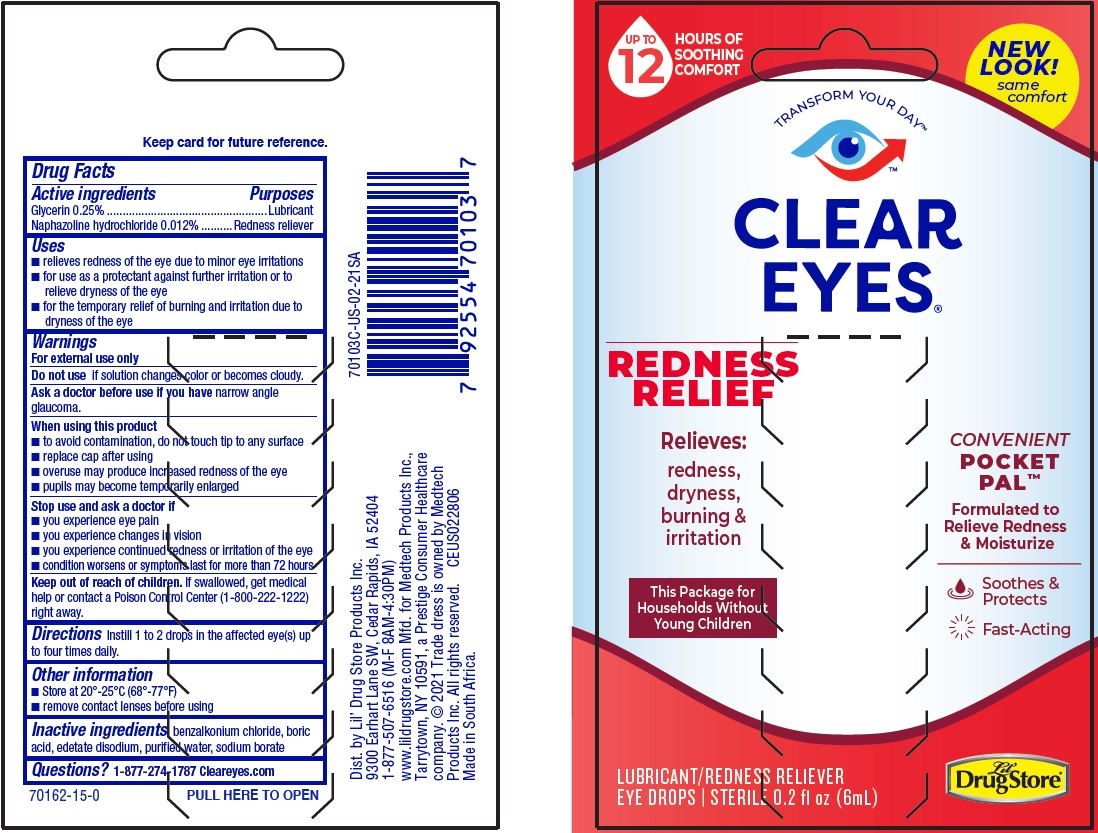 DRUG LABEL: Cleareyes Redness Relief
NDC: 66715-7010 | Form: LIQUID
Manufacturer: Lil' Drug Store Products, Inc.
Category: otc | Type: HUMAN OTC DRUG LABEL
Date: 20231215

ACTIVE INGREDIENTS: NAPHAZOLINE HYDROCHLORIDE 0.00012 mg/1 mL; GLYCERIN 0.0025 mg/1 mL
INACTIVE INGREDIENTS: BENZALKONIUM CHLORIDE; BORIC ACID; EDETATE DISODIUM; WATER; SODIUM BORATE

Cleareyes® Redness Relief

Drug Facts

ACTIVE INGREDIENT

PURPOSE

Active ingredients | Purposes
Glycerin 0.25% | Lubricant
Naphazoline hydrochloride 0.012% | Redness reliever

Uses

- relieves redness of the eye due to minor eye irritations
- for use as a protectant against further irritation or to relieve dryness of the eye
- for the temporary relief of burning and irritation due to dryness of the eye

Warnings

For external use only

Do not use if solution changes color or becomes cloudy

Ask a doctor before use if you have narrow angle glaucoma

When using this product

- pupils may become enlarged temporarily
- overuse may produce increased redness of the eye
- remove contact lenses before use
- to avoid contamination, do not touch tip to any surface
- replace cap after using

Stop use and ask a doctor if

- you experience eye pain
- you experience changes in vision
- you experience continued redness or irritation of the eye
- the condition worsens or persists for more than 72 hours

Keep out of reach of children. If swallowed, get medical help or contact a Poison Control Center (1-800-222-1222) right away.

Directions

Instill 1 to 2 drops in the affected eye(s) up to four times daily.

Other information

Store at room temperature

Inactive ingredients

benzalkonium chloride, boric acid, edetate disodium, purified water, sodium borate

Questions?

1-877-274-1787 www.cleareyes.com

Distributed by Lil' Drug Store Products Inc.
9300 Earhart Lane SW, Cedar Rapids, IA 52404

PRINCIPAL DISPLAY PANEL - 6 mL Bottle Package (Canada)

UP TO

12

HOURS OF

SOOTHING

COMFORT

NEW

LOOK!

SAME

COMFORT

TRANSFORM YOUR DAY™

CLEAR

EYES®

REDNESS

RELIEF

Relieves:

redness,

dryness,

burning &

irritation

This Package for

Households Without

Young Children

CONVENIENT

POCKET

PAL™

Formulated to

Relieve Redness

& Moisturize

Soothes &

Protects

Fast-Acting

LUBRICANT/REDNESS RELIEVER

EYE DROPS | STERILE 0.2 fl oz (6mL)

[Lil' Drug Store logo]

PRINCIPAL DISPLAY PANEL - 6 mL Bottle Package - South Africa

UP TO

12

HOURS OF

SOOTHING

COMFORT

NEW

LOOK!

SAME

COMFORT

TRANSFORM YOUR DAY™

CLEAR

EYES®

REDNESS

RELIEF

Relieves:

redness,

dryness,

burning &

irritation

This Package for

Households Without

Young Children

CONVENIENT

POCKET

PAL™

Formulated to

Relieve Redness

& Moisturize

Soothes &

Protects

Fast-Acting

LUBRICANT/REDNESS RELIEVER

EYE DROPS | STERILE 0.2 fl oz (6mL)

[Lil' Drug Store logo]